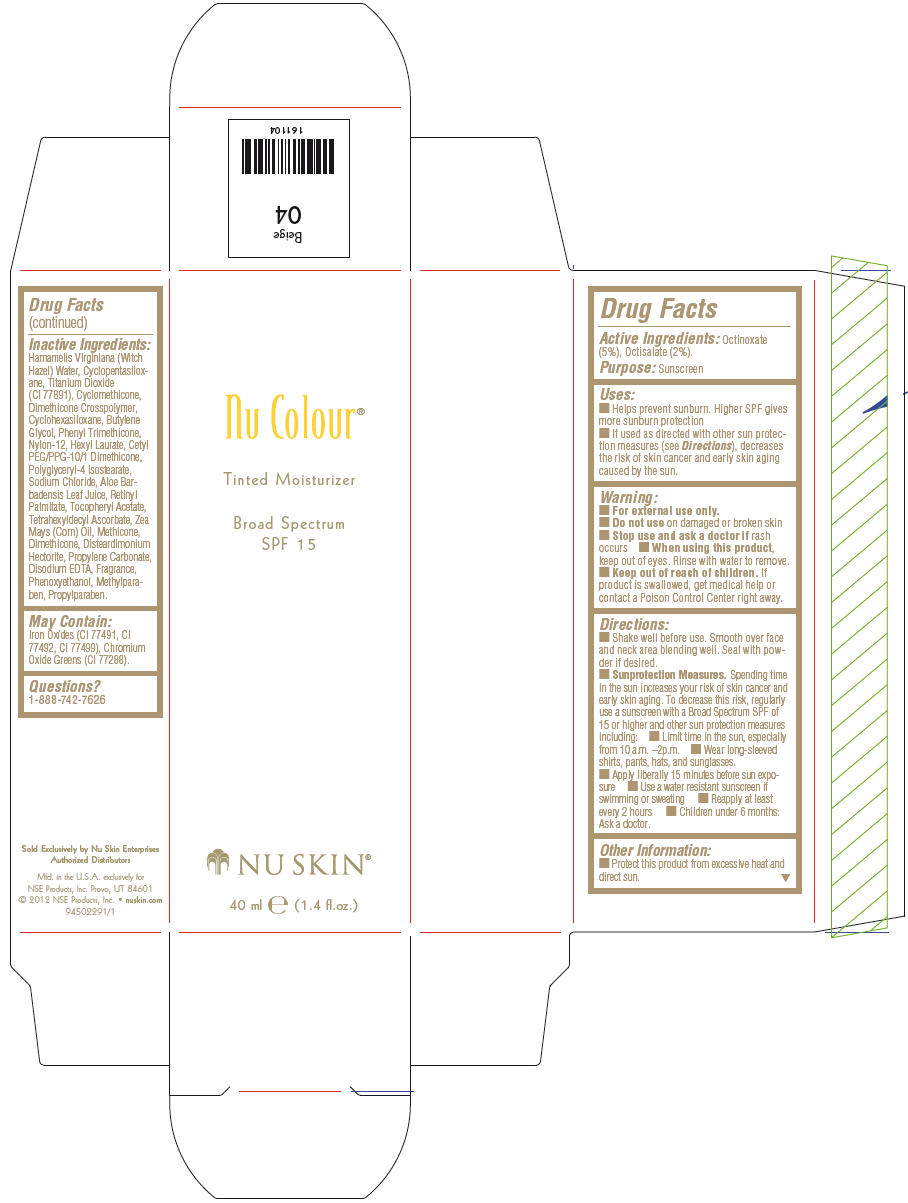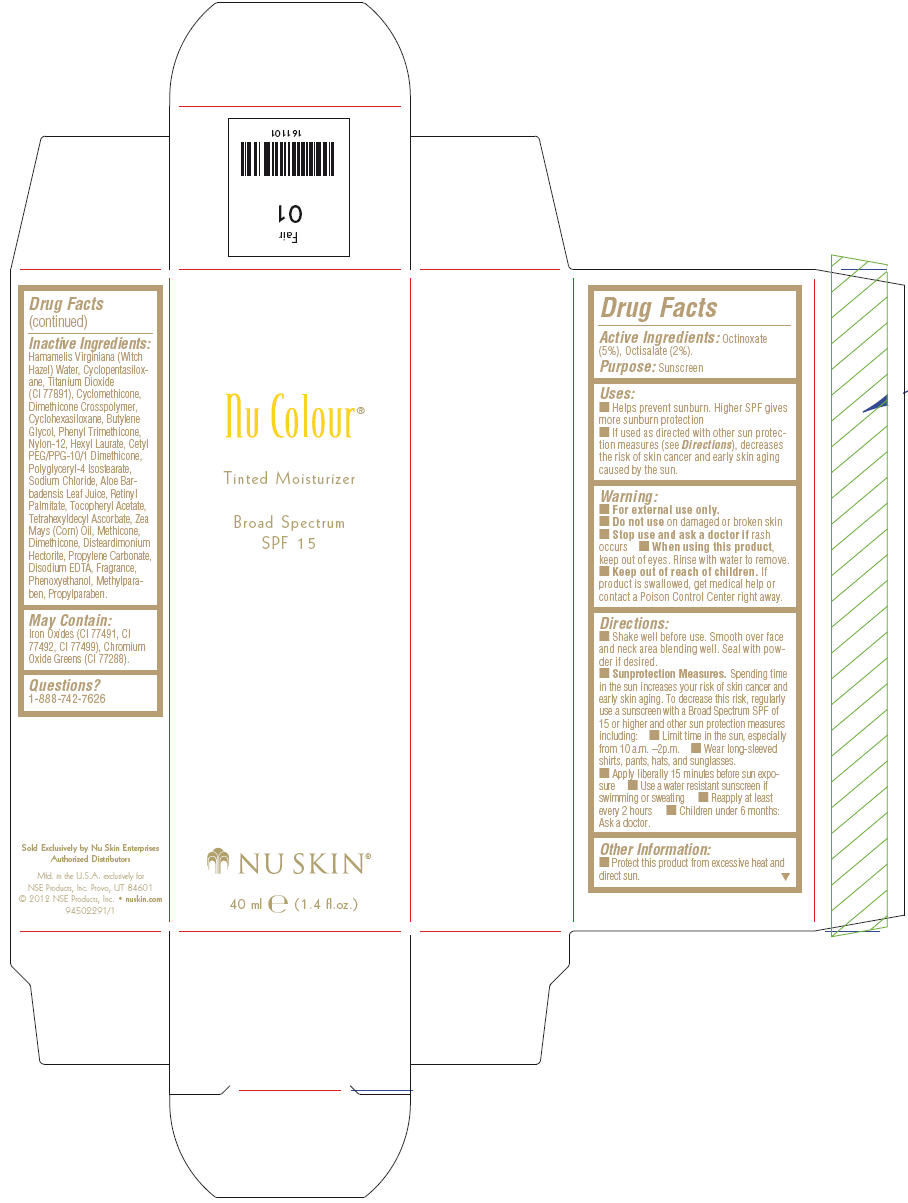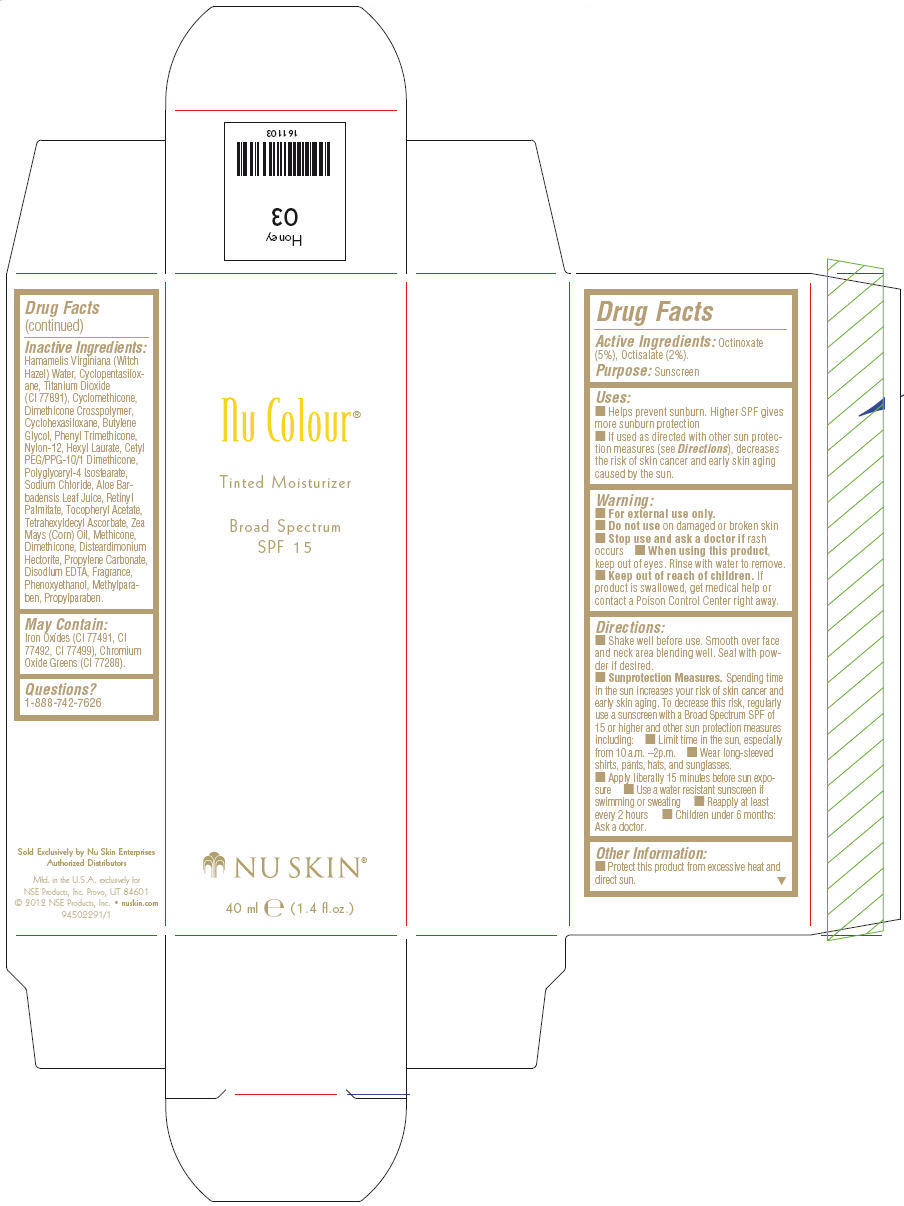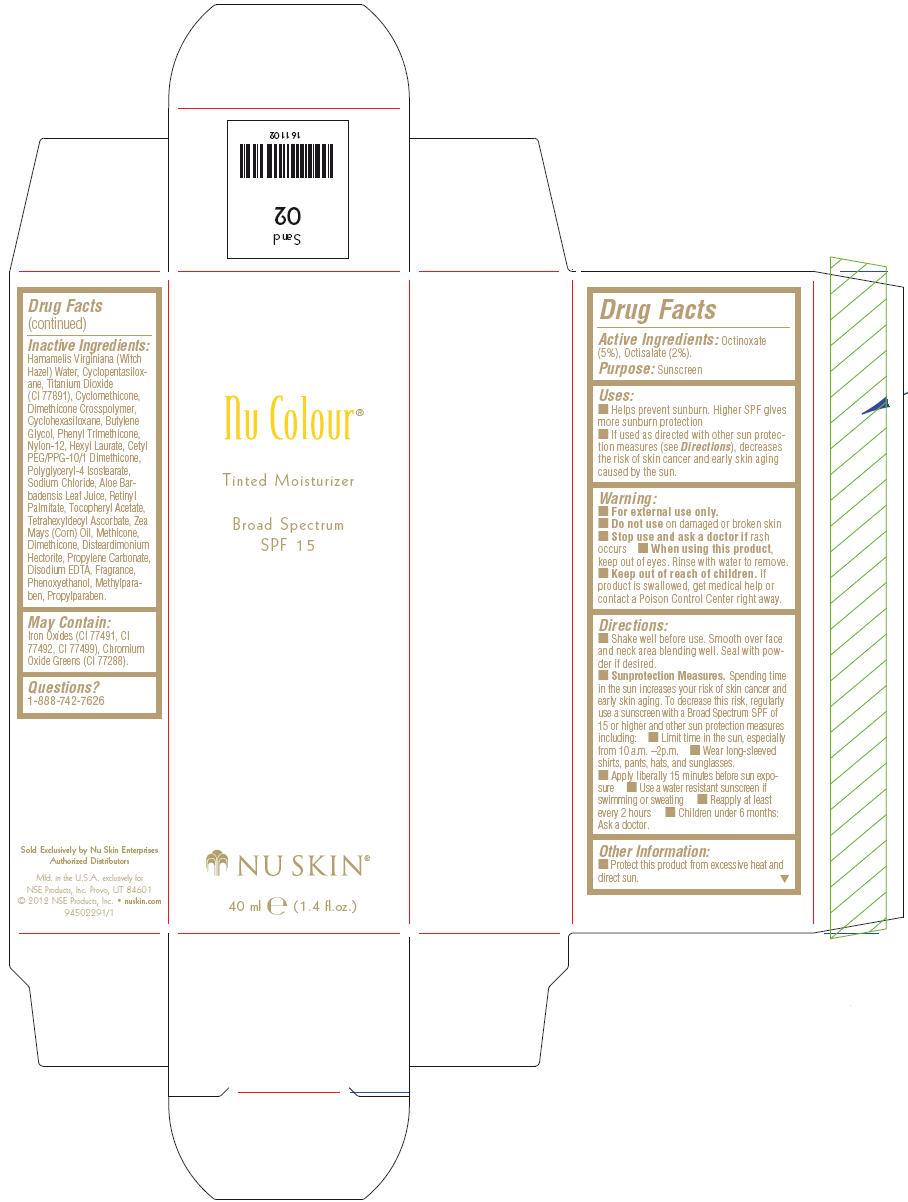 DRUG LABEL: Nu Skin Nu Colour 
NDC: 62839-1104 | Form: LOTION
Manufacturer: NSE Products, Inc.
Category: otc | Type: HUMAN OTC DRUG LABEL
Date: 20130619

ACTIVE INGREDIENTS: Octinoxate 50 mg/1 mL; Octisalate 20 mg/1 mL
INACTIVE INGREDIENTS: Hamamelis Virginiana Top Water; Cyclomethicone 5; Titanium Dioxide; Cyclomethicone; Cyclomethicone 6; Butylene Glycol; Phenyl Trimethicone; Nylon-12; Hexyl Laurate; Polyglyceryl-4 Isostearate; Sodium Chloride; Ferric Oxide Yellow; Phenoxyethanol; Disteardimonium Hectorite; Ferric Oxide Red; Ferrosoferric Oxide; Methylparaben; Propylene Carbonate; Dimethicone; Edetate Disodium; Propylparaben; Aloe Vera Leaf; Tetrahexyldecyl Ascorbate; .Alpha.-Tocopherol Acetate; Vitamin A Palmitate; Corn Oil; Chromic Oxide

Nu Skin® Nu Colour® Tinted Moisturizer Broad Spectrum SPF 15

Drug Facts

Active Ingredients

Octinoxate (5%), Octisalate (2%).

Purpose

Sunscreen

Uses

- Helps prevent sunburn. Higher SPF gives more sunburn protection
- If used as directed with other sun protection measures (see Directions), decreases the risk of skin cancer and early skin aging caused by the sun.

Warning

- For external use only.

- Do not use on damaged or broken skin

- Stop use and ask a doctor if rash occurs

- When using this product, keep out of eyes. Rinse with water to remove.

- Keep out of reach of children. If product is swallowed, get medical help or contact a Poison Control Center right away.

Directions

- Shake well before use. Smooth over face and neck area blending well. Seal with powder if desired.
- Sunprotection Measures. Spending time in the sun increases your risk of skin cancer and early skin aging. To decrease this risk, regularly use a sunscreen with a Broad Spectrum SPF of 15 or higher and other sun protection measures including:
  - Limit time in the sun, especially from 10 a.m. –2p.m.
  - Wear long-sleeved shirts, pants, hats, and sunglasses.
  - Apply liberally 15 minutes before sun exposure
  - Use a water resistant sunscreen if swimming or sweating
  - Reapply at least every 2 hours
  - Children under 6 months: Ask a doctor.

Other Information

- Protect this product from excessive heat and direct sun.

Inactive Ingredients

Hamamelis Virginiana (Witch Hazel) Water, Cyclopentasiloxane, Titanium Dioxide (Cl 77891), Cyclomethicone, Dimethicone Crosspolymer, Cyclohexasiloxane, Butylene Glycol, Phenyl Trimethicone, Nylon-12, Hexyl Laurate, Cetyl PEG/PPG-10/1 Dimethicone, Polyglyceryl-4 Isostearate, Sodium Chloride, Aloe Barbadensis Leaf Juice, Retinyl Palmitate, Tocopheryl Acetate, Tetrahexyldecyl Ascorbate, Zea Mays (Corn) Oil, Methicone, Dimethicone, Disteardimonium Hectorite, Propylene Carbonate, Disodium EDTA, Fragrance, Phenoxyethanol, Methylparaben, Propylparaben.

May Contain

Iron Oxides (CI 77491, CI 77492, CI 77499), Chromium Oxide Greens (CI 77288).

Questions?

1-888-742-7626

PRINCIPAL DISPLAY PANEL - 40 ml Bottle Carton (Beige)

Nu Colour®

Tinted Moisturizer

Broad Spectrum
SPF 15

NU SKIN®

40 ml e (1.4 fl.oz.)

PRINCIPAL DISPLAY PANEL - 40 ml Bottle Carton (Fair)

Nu Colour®

Tinted Moisturizer

Broad Spectrum
SPF 15

NU SKIN®

40 ml e (1.4 fl.oz.)

PRINCIPAL DISPLAY PANEL - 40 ml Bottle Carton (Honey)

Nu Colour®

Tinted Moisturizer

Broad Spectrum
SPF 15

NU SKIN®

40 ml e (1.4 fl.oz.)

PRINCIPAL DISPLAY PANEL - 40 ml Bottle Carton (Sand)

Nu Colour®

Tinted Moisturizer

Broad Spectrum
SPF 15

NU SKIN®

40 ml e (1.4 fl.oz.)